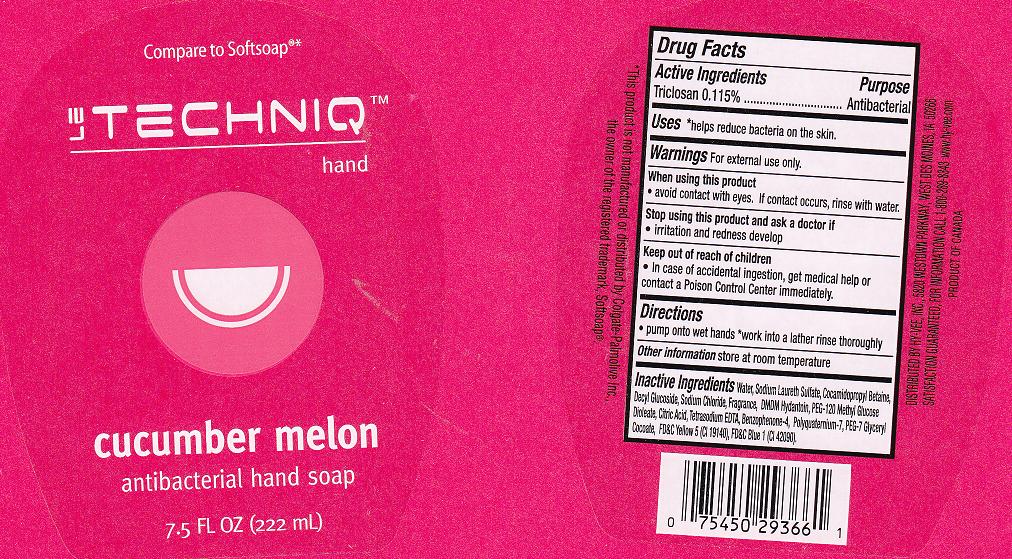 DRUG LABEL: ANTIBACTERIAL
NDC: 42507-295 | Form: LIQUID
Manufacturer: HYVEE INC
Category: otc | Type: HUMAN OTC DRUG LABEL
Date: 20110609

ACTIVE INGREDIENTS: TRICLOSAN 0.115 mL/100 mL
INACTIVE INGREDIENTS: WATER; SODIUM LAURETH SULFATE; COCAMIDOPROPYL BETAINE; SODIUM CHLORIDE; DECYL GLUCOSIDE; DMDM HYDANTOIN; PEG-120 METHYL GLUCOSE DIOLEATE; EDETATE SODIUM; CITRIC ACID MONOHYDRATE; SULISOBENZONE; POLYQUATERNIUM-7 (70/30 ACRYLAMIDE/DADMAC; 1600 KD); GLYCERYL COCOATE; FD&C YELLOW NO. 5; FD&C BLUE NO. 1

DRUG FACTS

ACTIVE INGREDIENT

TRICLOSAN 0.115%

PURPOSE

ANTIBACTERIAL

USES

HELPS REDUCE BACTERIA ON THE SKIN

WARNINGS

FOR EXTERNAL USE ONLY.

WHEN USING THIS PRODUCT

AVOID CONTACT WITH EYES. IF CONTACT OCCURS, RINSE WITH WATER.

STOP USING THIS PRODUCT AND ASK A DOCTOR IF

IRRITATION AND REDNESS DEVELOP.

KEEP OUT REACH OF CHILDREN

IN CASE OF ACCIDENTAL INGESTION, GET MEDICAL HELP OR CONTACT A POISON CONTROL CENTER IMMEDIATELY.

DIRECTIONS

PUMP ONTO WET HANDS. WORK INTO A LATHER RINSE THROUGHLY.

OTHER INFORMATION

STORE AT ROOM TEMPERATURE.

INACTIVE INGREDIENTS

WATER, SODIUM LAURETH SULFATE, COCAMIDOPROPYL BETAINE, DECYL GLUCOSIDE, SODIUM CHLORIDE, FRAGRANCE, DMDM HYDANTOIN, PEG-120 METHYL GLUCOSE DIOLEATE, CITRIC ACID, SODIUM SULFATE, TETRASODIUM EDTA, BENZOPHENONE-4, POLYQUATERNIUM-7, PEG-7 GLYCERYL COCOATE, YELLOW 5 (CI 19140), BLUE 1 (CI 42090).